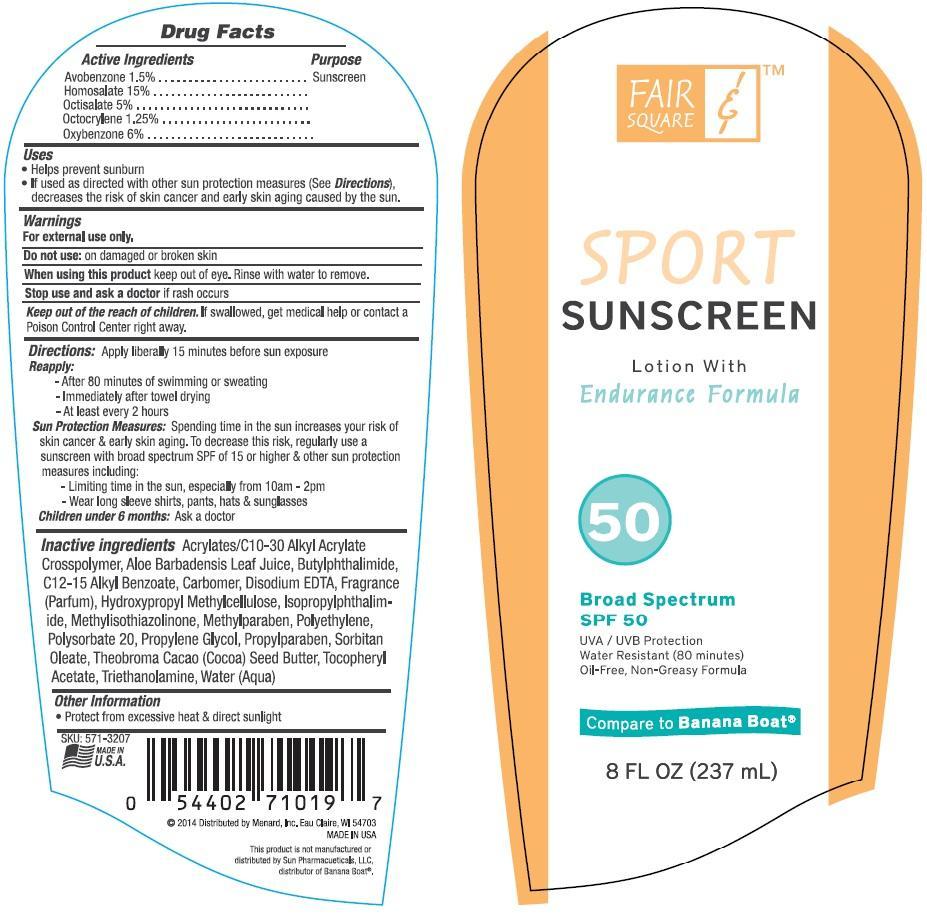 DRUG LABEL: Fair and Square
NDC: 58443-0152 | Form: LOTION
Manufacturer: Prime Enterprises, Inc.
Category: otc | Type: HUMAN OTC DRUG LABEL
Date: 20200117

ACTIVE INGREDIENTS: AVOBENZONE 15 mg/1 mL; HOMOSALATE 150 mg/1 mL; OCTISALATE 50 mg/1 mL; OCTOCRYLENE 12.5 mg/1 mL; OXYBENZONE 60 mg/1 mL
INACTIVE INGREDIENTS: C10-30 CHOLESTEROL/LANOSTEROL ESTERS; ALOE VERA LEAF; N-BUTYLPHTHALIMIDE; ISOPROPYLPHTHALIMIDE; ALKYL (C12-15) BENZOATE; CARBOMER HOMOPOLYMER TYPE C (ALLYL PENTAERYTHRITOL CROSSLINKED); EDETATE DISODIUM; HYPROMELLOSES; METHYLISOTHIAZOLINONE; METHYLPARABEN; HIGH DENSITY POLYETHYLENE; POLYHYDROXYSTEARIC ACID (2300 MW); POLYSORBATE 20; PROPYLENE GLYCOL; PROPYLPARABEN; PEG-6 SORBITAN OLEATE; COCOA BUTTER; .ALPHA.-TOCOPHEROL ACETATE; TROLAMINE; WATER

Active ingredients

Avobenzone 1.5%, Homosalate 15%, Octisalate 5%, Octocrylene 1.25%, and Oxybenzone 6%

Purpose

Sunscreen

Uses

- helps prevent sunburn
- if used as directed with other sun protection measures (See Directions), decreases the risk of skin cancer and early skin aging caused by the sun.

Warnings

OTHER SAFETY INFORMATION

For external use only.

Do not use: on damaged or broken skin.

When using this product keep out of eyes. Rinse with water to remove.

Stop use and ask a doctor if rash occurs.

Keep out of reach of children. If swallowed, get medical help or contact a Poison Control Center right away.

Directions: apply liberally 15 minutes before sun exposure

reapply:

- after 80 minutes of swimming or sweating
- Immediately after towel drying
- at least every 2 hours

Sun Protection Measures: Spending time in the sun increases your risk of skin cancer & early skin aging. To decrease this risk, regularly use a sunscreen with a broad spectrum SPF of 15 or higher & other sun protection measures including:

- limit time in the sun, especially from 10 a.m. – 2 p.m.
- wear long-sleeve shirts, pants, hats, and sunglasses

Children under 6 months: Ask a doctor

Inactive Ingredients

Acrylates/C10-30 Alkyl Acrylate Crosspolymer, Aloe Barbadensis Leaf Juice, Butylphthalimide, C12-15 Alkyl Benzoate, Carbomer, Disodium EDTA, Fragrance (Parfum), Hydroxypropyl Methylcellulose, Isopropylphthalimide, Methylisothiazolinone, Methylparaben, Polyethylene, Polysorbate 20, Propylene Glycol, Propylparaben, Sorbitan Oleate, Theobroma Cacao (Cocoa) Seed Butter, Tocopheryl Acetate, Triethanolamine, Water (Aqua)

Other information

- protect from excesive heat & direct sunlight

PRINCIPAL DISPLAY PANEL - 237 mL Bottle Label

FAIR

&

SQUARE

SPORT

SUNSCREEN

Lotion With

Endurance Formula

50

Broad Spectrum

SPF 50

UVA/UVB Protection

Water Resistant (80 minutes)

Oil-Free, Non-Greasy Formula

Compare to Banana Boat

8 FL OZ (237mL)